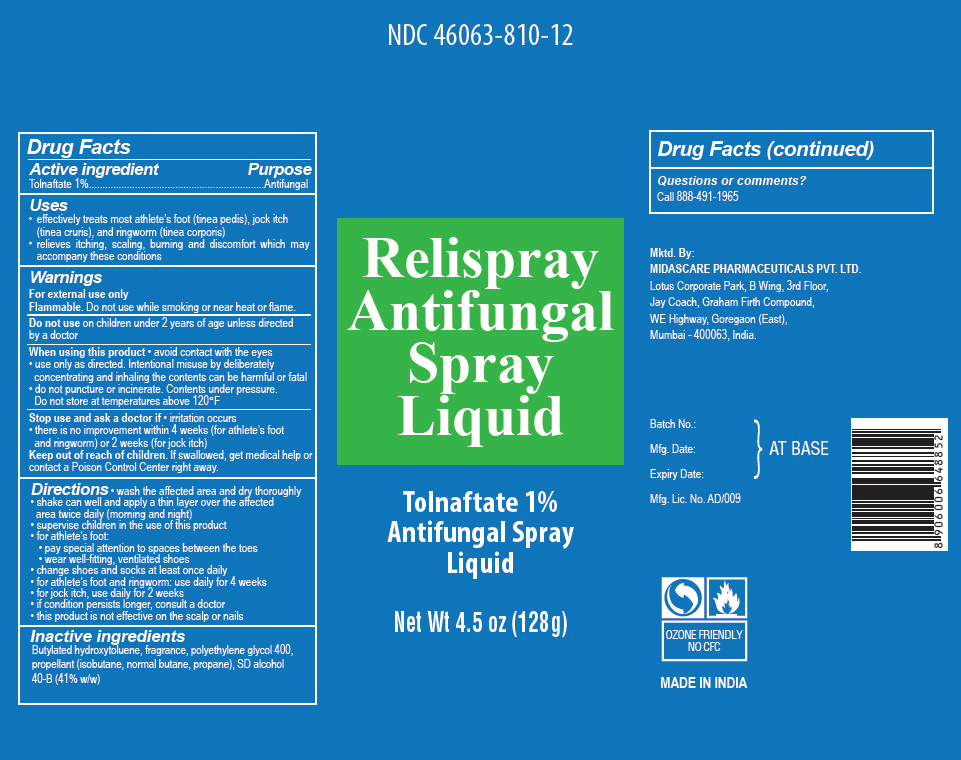 DRUG LABEL: Relispray Antifungal Liquid
NDC: 46063-810 | Form: AEROSOL, SPRAY
Manufacturer: Midas-Care Pharmaceuticals Pvt. Ltd.
Category: otc | Type: HUMAN OTC DRUG LABEL
Date: 20241217

ACTIVE INGREDIENTS: Tolnaftate 0.01 g/1 g
INACTIVE INGREDIENTS: Butylated hydroxytoluene; FRAGRANCE CLEAN ORC0600327; Polyethylene glycol 400; LIQUEFIED PETROLEUM GAS; ALCOHOL

Relispray Antifungal Spray Liquid

Drug Facts

Active ingredient

Tolnaftate 1%

Purpose

Antifungal

Uses

- effectively treats most athlete's foot (tinea pedis), jock itch (tinea cruris), and ringworm (tinea corporis)
- relieves itching, scaling, burning and discomfort which may accompany these conditions

Warnings

For external use only

Flammable. Do not use while smoking or near heat or flame.

Do not use on children under 2 years of age unless directed by a doctor

When using this product

- avoid contact with the eyes
- use only as directed. Intentional misuse by deliberately concentrating and inhaling the contents can be harmful or fatal
- do not puncture or incinerate. Contents under pressure.
  Do not store at temperatures above 120°F

Stop use and ask a doctor if

- irritation occurs
- there is no improvement within 4 weeks (for athlete's foot and ringworm) or 2 weeks (for jock itch)

Keep out of reach of children. If swallowed, get medical help or contact a Poison Control Center right away.

Directions

- wash the affected area and dry thoroughly
- shake can well and apply a thin layer over the affected area twice daily (morning and night)
- supervise children in the use of this product
- for athlete's foot:
  - pay special attention to spaces between the toes
  - wear well-fitting, ventilated shoes
- change shoes and socks at least once daily
- for athlete's foot and ringworm: use daily for 4 weeks
- for jock itch, use daily for 2 weeks
- if condition persists longer, consult a doctor
- this product is not effective on the scalp or nails

Inactive ingredients

Butylated hydroxytoluene, fragrance, polyethylene glycol 400, propellant (isobutane, normal butane, propane), SD alcohol 40-B (41% w/w)

Questions or comments?

Call 888-491-1965

PRINCIPAL DISPLAY PANEL - 128 g Can Label

NDC 46063-810-12

Relispray
Antifungal
Spray
Liquid

Tolnaftate 1%
Antifungal Spray
Liquid

Net Wt 4.5 oz (128g)